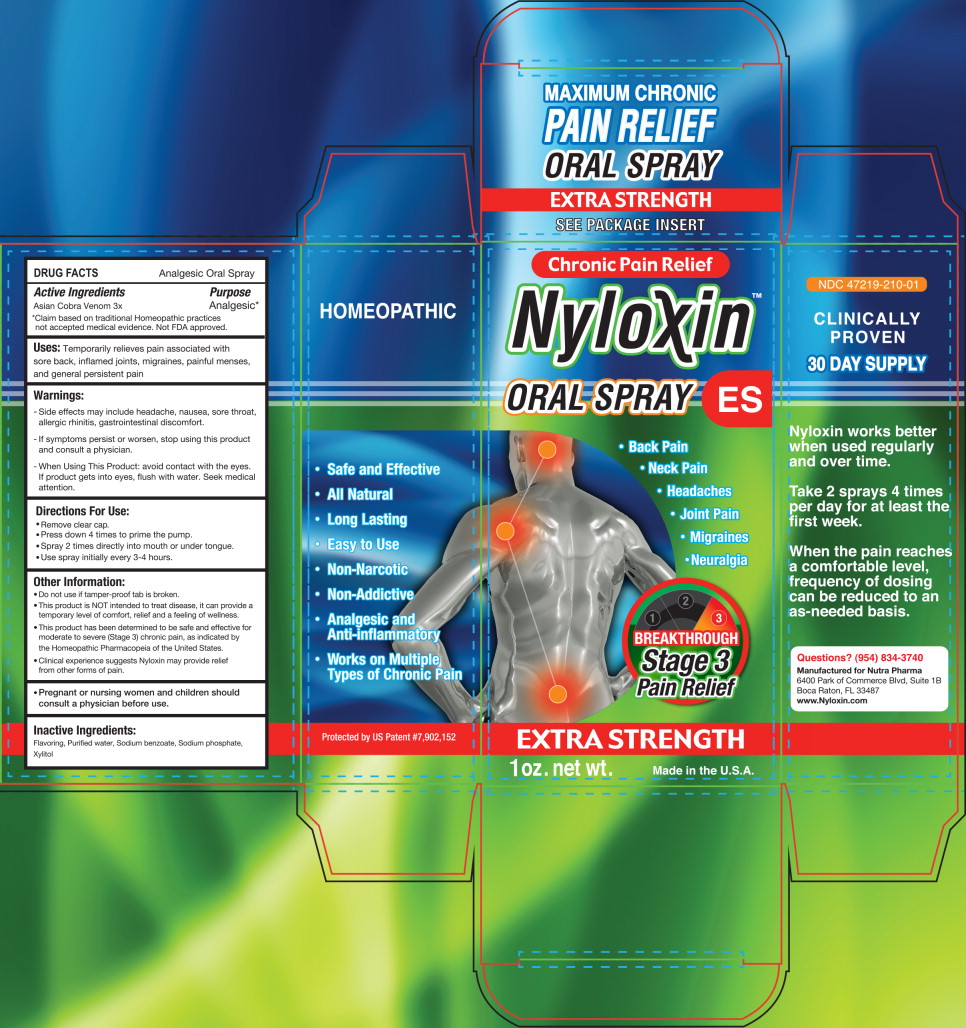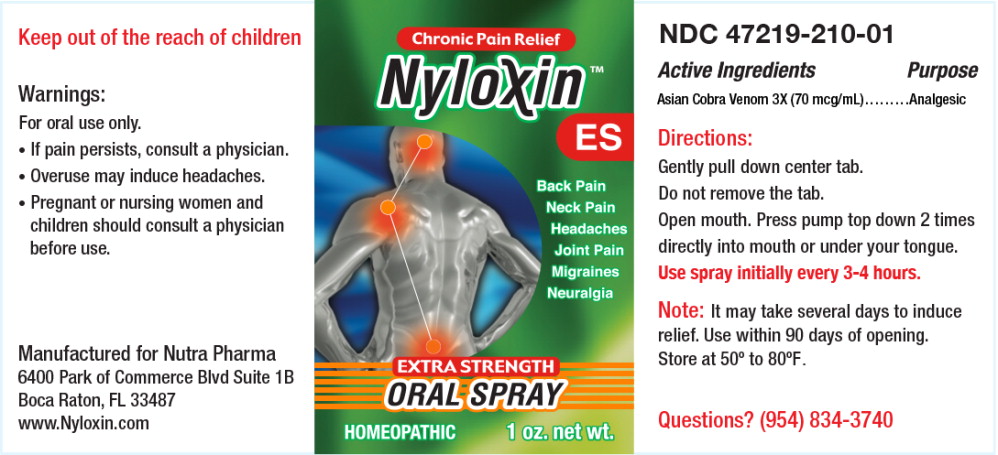 DRUG LABEL: Nyloxin

NDC: 47219-210 | Form: SPRAY, METERED
Manufacturer: Nutra Pharma Corporation
Category: homeopathic | Type: HUMAN OTC DRUG LABEL
Date: 20251020

ACTIVE INGREDIENTS: NAJA NAJA VENOM 3 [hp_X]/1 mL
INACTIVE INGREDIENTS: WATER; SODIUM BENZOATE; SODIUM PHOSPHATE; XYLITOL

DRUG FACTS

Analgesic Topical Gel

Active Ingredients

Asian Cobra Venom 4x

Purpose

Analgesic*

*Claim based on traditional Homeopathic practices not accepted medical evidence. Not FDA approved.

Uses:

Temporarily relieves pain associated with sore back, inflamed joints, migraines, painful menses, and general persistent pain

Warnings:

- Side effects may include headache, nausea, sore throat, allergic rhinitis, gastrointestinal discomfort.
- If symptoms persist or worsen, stop using this product and consult a physician.
- When Using This Product: avoid contact with the eyes. If product gets into eyes, flush with water. Seek medical attention.

Directions For Use:

- Remove clear cap.
- Press down 4 times to prime the pump.
- Spray 2 times directly into mouth or under tongue.
- Use spray initially every 3-4 hours.

Other Information:

- Do not use if tamper-proof tab is broken.
- This product is NOT intended to treat disease, it can provide a temporary level of comfort, relief and a feeling of wellness.
- Th s product has been determined to be safe and effective for moderate to severe (Stage 3) chronic pain, as indicated by the Homeopathic Pharmacopeia of the United States.
- Clinical experience suggests Nyloxin may provide relief from other forms of pain.

KEEP OUT OF REACH OF CHILDREN

- Pregnant or nursing women and children should consult a physician before use.

Inactive Ingredients:

Flavoring, Purified water, Sodium benzoate, Sodium phosphate, Xylitol

Principal Display Panel - 1 oz Carton Label

Chronic Pain Relief

Nyloxin™

ORAL SPRAY ES

• Back Pain
• Neck Pain
• Headaches
• Join Pain
• Migraines
• Neuralgia

BREAKTHROUGH
Stage 3
Pain Relief

EXTRA STRENGTH

1 oz. net wt.

Made in the U.S.A.

Principal Display Panel - 1 oz Bottle Label

Chronic Pain Relief

Nyloxin™
ES

• Back Pain
• Neck Pain
• Headaches
• Join Pain
• Migraines
• Neuralgia

EXTRA STRENGTH
ORAL SPRAY

HOMEOPATHIC

1 oz. net wt.